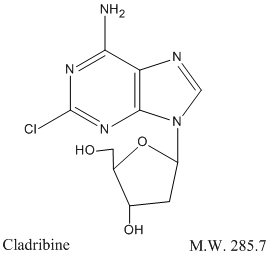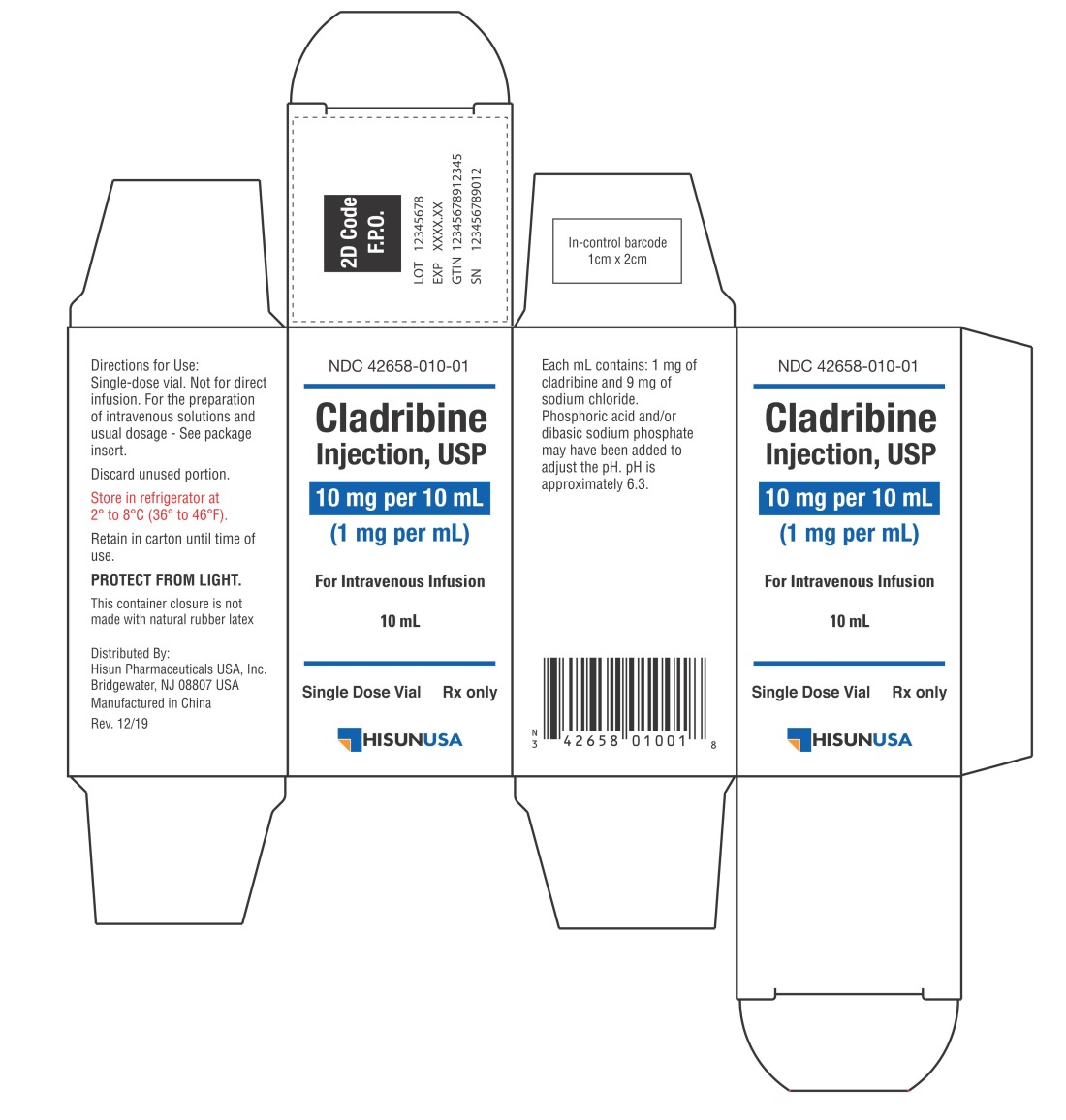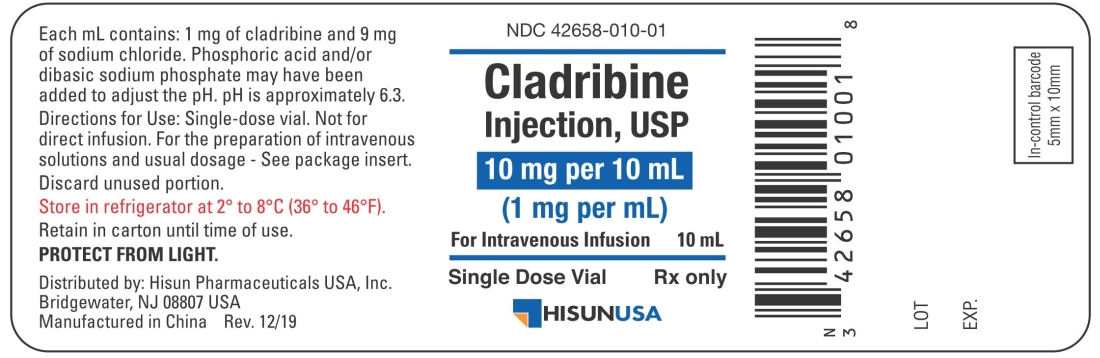 DRUG LABEL: Cladribine
NDC: 42658-010 | Form: INJECTION, SOLUTION
Manufacturer: Hisun Pharmaceuticals USA, Inc.
Category: prescription | Type: HUMAN PRESCRIPTION DRUG LABEL
Date: 20251223

ACTIVE INGREDIENTS: CLADRIBINE 1 mg/1 mL
INACTIVE INGREDIENTS: SODIUM CHLORIDE 9 mg/1 mL; PHOSPHORIC ACID; SODIUM PHOSPHATE DIBASIC DIHYDRATE; WATER

Cladribine Injection, USP
For Intravenous Infusion Only
Rx only

WARNING

Cladribine injection should be administered under the supervision of a qualified physician experienced in the use of antineoplastic therapy. Suppression of bone marrow function should be anticipated. This is usually reversible and appears to be dose dependent. Serious neurological toxicity (including irreversible paraparesis and quadraparesis) has been reported in patients who received cladribine injection by continuous infusion at high doses (4 to 9 times the recommended dose for Hairy Cell Leukemia). Neurologic toxicity appears to demonstrate a dose relationship; however, severe neurological toxicity has been reported rarely following treatment with standard cladribine dosing regimens.

Acute nephrotoxicity has been observed with high doses of cladribine (4 to 9 times the recommended dose for Hairy Cell Leukemia), especially when given concomitantly with other nephrotoxic agents/therapies.

DESCRIPTION

Cladribine Injection, USP (also commonly known as 2-chloro-2΄-deoxy- β -D-adenosine) is a synthetic antineoplastic agent for continuous intravenous infusion. It is a clear, colorless, sterile, preservative-free, isotonic solution. Cladribine injection, USP is available in single-dose vials containing 10 mg (1 mg/mL) of cladribine, a chlorinated purine nucleoside analog. Each milliliter of cladribine injection, USP contains 1 mg of the active ingredient and 9 mg (0.15 mEq) of sodium chloride as an inactive ingredient. The solution has a pH range of 5.5 to 8.0. Phosphoric acid and/or dibasic sodium phosphate may have been added to adjust the pH to 6.3±0.3.

The chemical name for cladribine is 2-chloro-6-amino-9-(2-deoxy-β-D-erythropento-furanosyl) purine and the structure is represented below:

CLINICAL PHARMACOLOGY

Cellular Resistance and Sensitivity

The selective toxicity of 2-chloro-2΄-deoxy-β-D-adenosine towards certain normal and malignant lymphocyte and monocyte populations is based on the relative activities of deoxycytidine kinase and deoxynucleotidase. Cladribine passively crosses the cell membrane. In cells with a high ratio of deoxycytidine kinase to deoxynucleotidase, it is phosphorylated by deoxycytidine kinase to 2-chloro-2΄-deoxy- β -D-adenosine monophosphate (2-CdAMP). Since 2-chloro-2΄-deoxy- β -D-adenosine is resistant to deamination by adenosine deaminase and there is little deoxynucleotide deaminase in lymphocytes and monocytes, 2-CdAMP accumulates intracellularly and is subsequently converted into the active triphosphate deoxynucleotide, 2-chloro-2΄-deoxy- β -D-adenosine triphosphate (2-CdATP). It is postulated that cells with high deoxycytidine kinase and low deoxynucleotidase activities will be selectively killed by 2-chloro-2΄-deoxy- β -D-adenosine as toxic deoxynucleotides accumulate intracellularly.

Cells containing high concentrations of deoxynucleotides are unable to properly repair single-strand DNA breaks. The broken ends of DNA activate the enzyme poly (ADP-ribose) polymerase resulting in NAD and ATP depletion and disruption of cellular metabolism. There is evidence, also, that 2-CdATP is incorporated into the DNA of dividing cells, resulting in impairment of DNA synthesis. Thus, 2-chloro-2΄-deoxy- β -D-adenosine can be distinguished from other chemotherapeutic agents affecting purine metabolism in that it is cytotoxic to both actively dividing and quiescent lymphocytes and monocytes, inhibiting both DNA synthesis and repair.

Pharmacokinetics

In a clinical investigation, 17 patients with Hairy Cell Leukemia and normal renal function were treated for 7 days with the recommended treatment regimen of cladribine injection (0.09 mg/kg/day) by continuous intravenous infusion. The mean steady-state serum concentration was estimated to be 5.7 ng/mL with an estimated systemic clearance of 663.5 mL/h/kg when cladribine was given by continuous infusion over 7 days. In Hairy Cell Leukemia patients, there does not appear to be a relationship between serum concentrations and ultimate clinical outcome.

In another study, 8 patients with hematologic malignancies received a two (2) hour infusion of cladribine injection (0.12 mg/kg). The mean end-of-infusion plasma cladribine concentration was 48±19 ng/mL. For 5 of these patients, the disappearance of cladribine could be described by either a biphasic or triphasic decline. For these patients with normal renal function, the mean terminal half-life was 5.4 hours. Mean values for clearance and steady-state volume of distribution were 978±422 mL/h/kg and 4.5±2.8 L/kg, respectively.

Cladribine plasma concentration after intravenous administration declines multi-exponentially with an average half-life of 6.7 +/- 2.5 hours. In general, the apparent volume of distribution of cladribine is approximately 9 L/kg, indicating an extensive distribution in body tissues.

Cladribine penetrates into cerebrospinal fluid. One report indicates that concentrations are approximately 25% of those in plasma.

Cladribine is bound approximately 20% to plasma proteins.

Except for some understanding of the mechanism of cellular toxicity, no other information is available on the metabolism of cladribine in humans. An average of 18% of the administered dose has been reported to be excreted in urine of patients with solid tumors during a 5-day continuous intravenous infusion of 3.5–8.1 mg/m^2/day of cladribine. The effect of renal and hepatic impairment on the elimination of cladribine has not been investigated in humans.

CLINICAL STUDIES

Two single-center open label studies of cladribine injection have been conducted in patients with Hairy Cell Leukemia with evidence of active disease requiring therapy. In the study conducted at the Scripps Clinic and Research Foundation (Study A), 89 patients were treated with a single course of cladribine injection given by continuous intravenous infusion for 7 days at a dose of 0.09 mg/kg/day. In the study conducted at the M.D. Anderson Cancer Center (Study B), 35 patients were treated with a 7-day continuous intravenous infusion of cladribine injection at a comparable dose of 3.6 mg/m^2/day. A complete response (CR) required clearing of the peripheral blood and bone marrow of hairy cells and recovery of the hemoglobin to 12 g/dL, platelet count to 100 × 10^9/L, and absolute neutrophil count to 1500 × 10^6/L. A good partial response (GPR) required the same hematologic parameters as a complete response, and that fewer than 5% hairy cells remain in the bone marrow. A partial response (PR) required that hairy cells in the bone marrow be decreased by at least 50% from baseline and the same response for hematologic parameters as for complete response. A pathologic relapse was defined as an increase in bone marrow hairy cells to 25% of pretreatment levels. A clinical relapse was defined as the recurrence of cytopenias, specifically, decreases in hemoglobin ≥ 2 g/dL, ANC ≥ 25% or platelet counts ≥ 50,000. Patients who met the criteria for a complete response but subsequently were found to have evidence of bone marrow hairy cells (< 25% of pretreatment levels) were reclassified as partial responses and were not considered to be complete responses with relapse.

Among patients evaluable for efficacy (N=106), using the hematologic and bone marrow response criteria described above, the complete response rates in patients treated with cladribine injection were 65% and 68% for Study A and Study B, respectively, yielding a combined complete response rate of 66%. Overall response rates (i.e., Complete plus Good Partial plus Partial Responses) were 89% and 86% in Study A and Study B, respectively, for a combined overall response rate of 88% in evaluable patients treated with cladribine injection.

Using an intent-to-treat analysis (N=123) and further requiring no evidence of splenomegaly as a criterion for CR (i.e., no palpable spleen on physical examination and ≤ 13 cm on CT scan), the complete response rates for Study A and Study B were 54% and 53%, respectively, giving a combined CR rate of 54%. The overall response rates (CR + GPR + PR) were 90% and 85%, for Studies A and B, respectively, yielding a combined overall response rate of 89%.

RESPONSE RATES TO CLADRIBINE TREATMENT IN PATIENTS WITH HAIRY CELL LEUKEMIA
 | CR | Overall
Evaluable Patients N=106 | 66% | 88%
Intent-to-treat Population N=123 | 54% | 89%

In these studies, 60% of the patients had not received prior chemotherapy for Hairy Cell Leukemia or had undergone splenectomy as the only prior treatment and were receiving cladribine as a first-line treatment. The remaining 40% of the patients received cladribine as a second-line treatment, having been treated previously with other agents, including α-interferon and/or deoxycoformycin. The overall response rate for patients without prior chemotherapy was 92%, compared with 84% for previously treated patients. Cladribine is active in previously treated patients; however, retrospective analysis suggests that the overall response rate is decreased in patients previously treated with splenectomy or deoxycoformycin and in patients refractory to α-interferon.

OVERALL RESPONSE RATES (CR + GPR + PR) TO CLADRIBINE TREATMENT IN PATIENTS WITH HAIRY CELL LEUKEMIA
 | OVERALL RESPONSE (N = 123) | NR + RELAPSE
No Prior Chemotherapy | 68/74 92% | 6 + 4 14%
Any Prior Chemotherapy | 41/49 84% | 8 + 3 22%
Previous Splenectomy | 32/41 [P < 0.05] 78% | 9 + 1 24%
Previous Interferon | 40/48 83% | 8 + 3 23%
Interferon Refractory | 6/11 55% | 5 + 2 64%
Previous Deoxycoformycin | 3/6 50% | 3 + 1 66%
NR = No Response

After a reversible decline, normalization of peripheral blood counts (Hemoglobin >12.0 g/dL, Platelets >100 × 10^9/L, Absolute Neutrophil Count (ANC) >1500 × 10^6/L) was achieved by 92% of evaluable patients. The median time to normalization of peripheral counts was 9 weeks from the start of treatment (Range: 2 to 72). The median time to normalization of Platelet Count was two weeks, the median time to normalization of ANC was 5 weeks and the median time to normalization of Hemoglobin was 8 weeks. With normalization of Platelet Count and Hemoglobin, requirements for platelet and RBC transfusions were abolished after Months 1 and 2, respectively, in those patients with complete response. Platelet recovery may be delayed in a minority of patients with severe baseline thrombocytopenia. Corresponding to normalization of ANC, a trend toward a reduced incidence of infection was seen after the third month, when compared to the months immediately preceding cladribine therapy. (see also WARNINGS, PRECAUTIONS and ADVERSE REACTIONS)

cladribine TREATMENT IN PATIENTS WITH HAIRY CELL LEUKEMIA TIME TO NORMALIZATION OF PERIPHERAL BLOOD COUNTS
Parameter | Median Time to Normalization of Count [Day 1 = First day of infusion]
Platelet Count | 2 weeks
Absolute Neutrophil Count | 5 weeks
Hemoglobin | 8 weeks
ANC, Hemoglobin and Platelet Count | 9 weeks

For patients achieving a complete response, the median time to response (i.e., absence of hairy cells in bone marrow and peripheral blood together with normalization of peripheral blood parameters), measured from treatment start, was approximately 4 months. Since bone marrow aspiration and biopsy were frequently not performed at the time of peripheral blood normalization, the median time to complete response may actually be shorter than that which was recorded. At the time of data cut-off, the median duration of complete response was greater than 8 months and ranged to 25+ months. Among 93 responding patients, seven had shown evidence of disease progression at the time of the data cut-off. In four of these patients, disease was limited to the bone marrow without peripheral blood abnormalities (pathologic progression), while in three patients there were also peripheral blood abnormalities (clinical progression). Seven patients who did not respond to a first course of cladribine received a second course of therapy. In the five patients who had adequate follow-up, additional courses did not appear to improve their overall response.

INDICATIONS FOR USE

Cladribine Injection, USP is indicated for the treatment of active Hairy Cell Leukemia as defined by clinically significant anemia, neutropenia, thrombocytopenia or disease-related symptoms.

CONTRAINDICATIONS

Cladribine Injection, USP is contraindicated in those patients who are hypersensitive to this drug or any of its components.

WARNINGS

Due to increased risk of infection in the setting of immunosuppression with chemotherapy including cladribine, it is recommended not to administer live attenuated vaccines to patients receiving cladribine injection.

Severe bone marrow suppression, including neutropenia, anemia and thrombocytopenia, has been commonly observed in patients treated with cladribine, especially at high doses. At initiation of treatment, most patients in the clinical studies had hematologic impairment as a manifestation of active Hairy Cell Leukemia. Following treatment with cladribine, further hematologic impairment occurred before recovery of peripheral blood counts began. During the first two weeks after treatment initiation, mean Platelet Count, ANC, and Hemoglobin concentration declined and subsequently increased with normalization of mean counts by Day 12, Week 5 and Week 8, respectively. The myelosuppressive effects of cladribine were most notable during the first month following treatment. Forty-four percent (44%) of patients received transfusions with RBCs and 14% received transfusions with platelets during Month 1. Careful hematologic monitoring, especially during the first 4 to 8 weeks after treatment with cladribine injection, is recommended (see PRECAUTIONS).

Fever (T ≥ 100°F) was associated with the use of cladribine in approximately two-thirds of patients (131/196) in the first month of therapy. Virtually all of these patients were treated empirically with parenteral antibiotics. Overall, 47% (93/196) of all patients had fever in the setting of neutropenia (ANC ≤ 1000), including 62 patients (32%) with severe neutropenia (i.e., ANC ≤ 500).

In a Phase I investigational study using cladribine in high doses (4 to 9 times the recommended dose for Hairy Cell Leukemia) as part of a bone marrow transplant conditioning regimen, which also included high dose cyclophosphamide and total body irradiation, acute nephrotoxicity and delayed onset neurotoxicity were observed. Thirty-one (31) poor-risk patients with drug-resistant acute leukemia in relapse (29 cases) or non-Hodgkins Lymphoma (2 cases) received cladribine for 7 to 14 days prior to bone marrow transplantation. During infusion, 8 patients experienced gastrointestinal symptoms. While the bone marrow was initially cleared of all hematopoietic elements, including tumor cells, leukemia eventually recurred in all treated patients. Within 7 to 13 days after starting treatment with cladribine, 6 patients (19%) developed manifestations of renal dysfunction (e.g., acidosis, anuria, elevated serum creatinine, etc.) and 5 required dialysis. Several of these patients were also being treated with other medications having known nephrotoxic potential. Renal dysfunction was reversible in 2 of these patients. In the 4 patients whose renal function had not recovered at the time of death, autopsies were performed; in 2 of these, evidence of tubular damage was noted. Eleven (11) patients (35%) experienced delayed onset neurologic toxicity. In the majority, this was characterized by progressive irreversible motor weakness (paraparesis/quadriparesis) of the upper and/or lower extremities, first noted 35 to 84 days after starting high dose therapy with cladribine. Non-invasive testing (electromyography and nerve conduction studies) was consistent with demyelinating disease. Severe neurologic toxicity has also been noted with high doses of another drug in this class.

Axonal peripheral polyneuropathy was observed in a dose escalation study at the highest dose levels (approximately 4 times the recommended dose for Hairy Cell Leukemia) in patients not receiving cyclophosphamide or total body irradiation. Severe neurological toxicity has been reported rarely following treatment with standard cladribine dosing regimens.

In patients with Hairy Cell Leukemia treated with the recommended treatment regimen (0.09 mg/kg/day for 7 consecutive days), there have been no reports of nephrologic toxicities.

Serious (e.g. respiratory infection, pneumonia and viral skin infections), including fatal infections (e.g. sepsis) were reported (see ADVERSE REACTIONS).

Of the 196 Hairy Cell Leukemia patients entered in the two trials, there were 8 deaths following treatment. Of these, 6 were of infectious etiology, including 3 pneumonias, and 2 occurred in the first month following cladribine therapy. Of the 8 deaths, 6 occurred in previously treated patients who were refractory to α interferon.

Benzyl alcohol is a constituent of the recommended diluent for the 7-day infusion solution. Benzyl alcohol has been reported to be associated with a fatal "Gasping Syndrome" in premature infants. (see DOSAGE AND ADMINISTRATION)

Pregnancy Category D

Cladribine can cause fetal harm when administered to a pregnant woman. Although there is no evidence of teratogenicity in humans due to cladribine, other drugs which inhibit DNA synthesis have been reported to be teratogenic in humans. Cladribine is teratogenic in animals. Advise females of reproductive potential to use highly effective contraception during treatment with cladribine. If cladribine is used during pregnancy, or if the patient becomes pregnant while taking this drug, the patient should be apprised of the potential hazard to the fetus.

Cladribine is teratogenic in mice and rabbits and consequently has the potential to cause fetal harm when administered to a pregnant woman. A significant increase in fetal variations was observed in mice receiving 1.5 mg/kg/day (4.5 mg/m^2) and increased resorptions, reduced litter size and increased fetal malformations were observed when mice received 3.0 mg/kg/day (9 mg/m^2). Fetal death and malformations were observed in rabbits that received 3.0 mg/kg/day (33.0 mg/m^2). No fetal effects were seen in mice at 0.5 mg/kg/day (1.5 mg/m^2) or in rabbits at 1.0 mg/kg/day (11.0 mg/m^2).

PRECAUTIONS

General

Cladribine injection is a potent antineoplastic agent with potentially significant toxic side effects. It should be administered only under the supervision of a physician experienced with the use of cancer chemotherapeutic agents. Patients undergoing therapy should be closely observed for signs of hematologic and non-hematologic toxicity. Periodic assessment of peripheral blood counts, particularly during the first 4 to 8 weeks post-treatment, is recommended to detect the development of anemia, neutropenia and thrombocytopenia and for early detection of any potential sequelae (e.g., infection or bleeding). As with other potent chemotherapeutic agents, monitoring of renal and hepatic function is also recommended, especially in patients with underlying kidney or liver dysfunction (see WARNINGS and ADVERSE REACTIONS).

Fever was a frequently observed side effect during the first month on study. Since the majority of fevers occurred in neutropenic patients, patients should be closely monitored during the first month of treatment and empiric antibiotics should be initiated as clinically indicated. Although 69% of patients developed fevers, less than 1/3 of febrile events were associated with documented infection. Given the known myelosuppressive effects of cladribine, practitioners should carefully evaluate the risks and benefits of administering this drug to patients with active infections (see WARNINGS and ADVERSE REACTIONS).

There are inadequate data on dosing of patients with renal or hepatic insufficiency. Development of acute renal insufficiency in some patients receiving high doses of cladribine has been described. Until more information is available, caution is advised when administering the drug to patients with known or suspected renal or hepatic insufficiency (see WARNINGS).

Rare cases of tumor lysis syndrome have been reported in patients treated with cladribine with other hematologic malignancies having a high tumor burden.

Cladribine injection must be diluted in designated intravenous solutions prior to administration (see DOSAGE AND ADMINISTRATION).

Laboratory Tests

During and following treatment, the patient's hematologic profile should be monitored regularly to determine the degree of hematopoietic suppression. In the clinical studies, following reversible declines in all cell counts, the mean Platelet Count reached 100 × 10^9/L by Day 12, the mean Absolute Neutrophil Count reached 1500 × 10^6/L by Week 5 and the mean Hemoglobin reached 12 g/dL by Week 8. After peripheral counts have normalized, bone marrow aspiration and biopsy should be performed to confirm response to treatment with cladribine. Febrile events should be investigated with appropriate laboratory and radiologic studies. Periodic assessment of renal function and hepatic function should be performed as clinically indicated.

Drug Interactions

There are no known drug interactions with cladribine injection. Caution should be exercised if cladribine injection is administered before, after, or in conjunction with other drugs known to cause immunosuppression or myelosuppression. (see WARNINGS)

Carcinogenesis

No animal carcinogenicity studies have been conducted with cladribine. However, its carcinogenic potential cannot be excluded based on demonstrated genotoxicity of cladribine.

Mutagenesis

As expected for compounds in this class, the actions of cladribine yield DNA damage. In mammalian cells in culture, cladribine caused the accumulation of DNA strand breaks. Cladribine was also incorporated into DNA of human lymphoblastic leukemia cells. Cladribine was not mutagenic in vitro (Ames and Chinese hamster ovary cell gene mutation tests) and did not induce unscheduled DNA synthesis in primary rat hepatocyte cultures. However, cladribine was clastogenic both in vitro (chromosome aberrations in Chinese hamster ovary cells) and in vivo (mouse bone marrow micronucleus test).

Impairment of Fertility

The effect on human fertility is unknown. When administered intravenously to Cynomolgus monkeys, cladribine has been shown to cause suppression of rapidly generating cells, including testicular cells.

Pregnancy

Pregnancy Category D

(see WARNINGS).

Nursing Mothers

It is not known whether this drug is excreted in human milk. Because many drugs are excreted in human milk and because of the potential for serious adverse reactions in nursing infants from cladribine, a decision should be made whether to discontinue nursing or discontinue the drug, taking into account the importance of the drug for the mother.

Pediatric Use

Safety and effectiveness in pediatric patients have not been established. In a Phase I study involving patients 1–21 years old with relapsed acute leukemia, cladribine was given by continuous intravenous infusion in doses ranging from 3 to 10.7 mg/m^2/day for 5 days (one-half to twice the dose recommended in Hairy Cell Leukemia). In this study, the dose-limiting toxicity was severe myelosuppression with profound neutropenia and thrombocytopenia. At the highest dose (10.7 mg/m^2/day), 3 of 7 patients developed irreversible myelosuppression and fatal systemic bacterial or fungal infections. No unique toxicities were noted in this study(1) (see WARNINGS and ADVERSE REACTIONS).

Geriatric Use

Clinical studies of cladribine did not include sufficient numbers of subjects age 65 and over to determine whether they respond differently from younger subjects. Other reported clinical experience has not identified differences in responses between the elderly and younger patients. In general, dose selection for an elderly patient should be cautious, reflecting the greater frequency of decreased hepatic, renal, or cardiac function, and of concomitant disease or other drug therapy in elderly patients.

ADVERSE REACTIONS

Clinical Trials Experience

Adverse drug reactions reported by ≥ 1% of cladribine-treated patients with HCL noted in the HCL clinical dataset (studies K90-091 and L91-048, n=576) are shown in the table below.

Adverse Drug Reactions in ≥ 1% of Patients Treated with Cladribine in HCL Clinical Trials
System Organ Class Preferred Term | Cladribine (n=576) %
Blood and Lymphatic System Disorder (see also sections WARNINGS and PRECAUTIONS)
Anemia | 1
Febrile neutropenia | 8
Psychiatric Disorders
Anxiety | 1
Insomnia | 3
Nervous System Disorders
Dizziness | 6
Headache | 14
Cardiac Disorders
Tachycardia | 2
Respiratory, Thoracic and Mediastinal Disorders
Breath sounds abnormal | 4
Cough | 7
Dyspnea [Dyspnea includes dyspnea, dyspnea exertional, and wheezing] | 5
Rales | 1
Gastrointestinal Disorders
Abdominal pain [Abdominal pain includes abdominal discomfort, abdominal pain, and abdominal pain (lower and upper)] | 4
Constipation | 4
Diarrhea | 7
Flatulence | 1
Nausea | 22
Vomiting | 9
Skin and Subcutaneous Tissue Disorders
Ecchymosis | 2
Hyperhidrosis | 3
Petechiae | 2
Pruritus | 2
Rash [Rash includes erythema, rash, and rash (macular, macula-papular, papular, pruritic, pustular and erythematous)] | 16
Musculoskeletal, Connective Tissue, and Bone Disorders
Arthralgia | 3
Myalgia | 6
Pain [Pain includes pain, back pain, chest pain, arthritis pain, bone pain, and pain in extremity] | 6
General Disorders and Administration Site Conditions (see also sections WARNINGS and PRECAUTIONS)
Administration site reaction [Administration site reaction includes administration site reaction, catheter site (cellulitis, erythema, hemorrhage, and pain), and infusion site reaction(erythema, edema, and pain)] | 11
Asthenia | 6
Chills | 2
Decreased appetite | 8
Fatigue | 31
Malaise | 5
Muscular weakness | 1
Edema peripheral | 2
Pyrexia | 33
Injury, Poisoning and Procedural Complications
Contusion | 1

The following safety data are based on 196 patients with Hairy Cell Leukemia: the original cohort of 124 patients plus an additional 72 patients enrolled at the same two centers after the original enrollment cutoff. In Month 1 of the Hairy Cell Leukemia clinical trials, severe neutropenia was noted in 70% of patients, fever in 69%, and infection was documented in 28%. Most non-hematologic adverse experiences were mild to moderate in severity.

Myelosuppression was frequently observed during the first month after starting treatment. Neutropenia (ANC < 500 × 10^6/L) was noted in 70% of patients, compared with 26% in whom it was present initially. Severe anemia (Hemoglobin < 8.5 g/dL) developed in 37% of patients, compared with 10% initially and thrombocytopenia (Platelets < 20 × 10^9/L) developed in 12% of patients, compared to 4% in whom it was noted initially.

During the first month, 54 of 196 patients (28%) exhibited documented evidence of infection. Serious infections (e.g., septicemia, pneumonia) were reported in 6% of all patients; the remainder were mild or moderate. Several deaths were attributable to infection and/or complications related to the underlying disease. During the second month, the overall rate of documented infection was 6%; these infections were mild to moderate and no severe systemic infections were seen. After the third month, the monthly incidence of infection was either less than or equal to that of the months immediately preceding cladribine therapy.

During the first month, 11% of patients experienced severe fever (i.e., ≥104°F). Documented infections were noted in fewer than one-third of febrile episodes. Of the 196 patients studied, 19 were noted to have a documented infection in the month prior to treatment. In the month following treatment, there were 54 episodes of documented infection: 23 (42%) were bacterial, 11 (20%) were viral and 11 (20%) were fungal. Seven (7) of 8 documented episodes of herpes zoster occurred during the month following treatment. Fourteen (14) of 16 episodes of documented fungal infections occurred in the first two months following treatment. Virtually all of these patients were treated empirically with antibiotics. (see WARNINGS and PRECAUTIONS)

Analysis of lymphocyte subsets indicates that treatment with cladribine is associated with prolonged depression of the CD4 counts. Prior to treatment, the mean CD4 count was 766/µL. The mean CD4 count nadir, which occurred 4 to 6 months following treatment, was 272/µL. Fifteen (15) months after treatment, mean CD4 counts remained below 500/µL. CD8 counts behaved similarly, though increasing counts were observed after 9 months. The clinical significance of the prolonged CD4 lymphopenia is unclear.

Another event of unknown clinical significance includes the observation of prolonged bone marrow hypocellularity. Bone marrow cellularity of < 35% was noted after 4 months in 42 of 124 patients (34%) treated in the two pivotal trials. This hypocellularity was noted as late as Day 1010. It is not known whether the hypocellularity is the result of disease related marrow fibrosis or if it is the result of cladribine toxicity. There was no apparent clinical effect on the peripheral blood counts.

The vast majority of rashes were mild. Most episodes of nausea were mild, not accompanied by vomiting, and did not require treatment with antiemetics. In patients requiring antiemetics, nausea was easily controlled, most frequently with chlorpromazine.

When used in other clinical settings the following ADRs were reported: bacteremia, cellulitis, localized infection, pneumonia, anemia, thrombocytopenia (with bleeding or petechiae), phlebitis, purpura, crepitations, localized edema and edema.

For a description of adverse reactions associated with use of high doses in non-Hairy Cell Leukemia patients, see WARNINGS.

Postmarketing Experience

The following additional adverse reactions have been reported since the drug became commercially available. These adverse reactions have been reported primarily in patients who received multiple courses of cladribine injection:

Infections and infestations: Septic shock. Opportunistic infections have occurred in the acute phase of treatment.

Blood and lymphatic system disorders: Bone marrow suppression with prolonged pancytopenia, including some reports of aplastic anemia; hemolytic anemia (including autoimmune hemolytic anemia), which was reported in patients with lymphoid malignancies, occurring within the first few weeks following treatment. Rare cases of myelodysplastic syndrome have been reported.

Immune system disorders: Hypersensitivity.

Metabolism and nutrition disorders: Tumor lysis syndrome.

Psychiatric disorders: Confusion (including disorientation).

Hepatobiliary disorders: Reversible, generally mild increases in bilirubin (uncommon) and transaminases.

Nervous System disorders: Depressed level of consciousness, neurological toxicity (including peripheral sensory neuropathy, motor neuropathy (paralysis), polyneuropathy, paraparesis); however, severe neurotoxicity has been reported rarely following treatment with standard cladribine dosing regimens.

Eye disorders: Conjunctivitis.

Respiratory, thoracic and mediastinal disorders: Pulmonary interstitial infiltrates (including lung infiltration, interstitial lung disease, pneumonitis and pulmonary fibrosis); in most cases, an infectious etiology was identified.

Skin and tissue disorders: Urticaria, hypereosinophilia; Stevens-Johnson. In isolated cases toxic epidermal necrolysis has been reported in patients who were receiving or had recently been treated with other medications (e.g., allopurinol or antibiotics) known to cause these syndromes.

Renal and urinary disorders: Renal failure (including renal failure acute, renal impairment).

OVERDOSAGE

High doses of cladribine have been associated with: irreversible neurologic toxicity (paraparesis/quadriparesis), acute nephrotoxicity, and severe bone marrow suppression resulting in neutropenia, anemia and thrombocytopenia (see WARNINGS). There is no known specific antidote to overdosage. Treatment of overdosage consists of discontinuation of cladribine, careful observation and appropriate supportive measures. It is not known whether the drug can be removed from the circulation by dialysis or hemofiltration.

DOSAGE AND ADMINISTRATION

Usual Dose

The recommended dose and schedule of cladribine injection, USP for active Hairy Cell Leukemia is as a single course given by continuous infusion for 7 consecutive days at a dose of 0.09 mg/kg/day. Deviations from this dosage regimen are not advised. If the patient does not respond to the initial course of cladribine injection, USP for Hairy Cell Leukemia, it is unlikely that they will benefit from additional courses. Physicians should consider delaying or discontinuing the drug if neurotoxicity or renal toxicity occurs (see WARNINGS).

Specific risk factors predisposing to increased toxicity from cladribine have not been defined. In view of the known toxicities of agents of this class, it would be prudent to proceed carefully in patients with known or suspected renal insufficiency or severe bone marrow impairment of any etiology. Patients should be monitored closely for hematologic and non-hematologic toxicity (see WARNINGS and PRECAUTIONS).

Preparation and Administration of Intravenous Solutions

Cladribine injection, USP must be diluted with the designated diluent prior to administration. Since the drug product does not contain any antimicrobial preservative or bacteriostatic agent, aseptic technique and proper environmental precautions must be observed in preparation of cladribine injection solutions.

To prepare a single daily dose

Cladribine injection, USP should be passed through a sterile 0.22µm disposable hydrophilic syringe filter prior to introduction into the infusion bag, prior to each daily infusion. Add the calculated dose (0.09 mg/kg or 0.09 mL/kg) of cladribine injection, USP through the sterile filter to an infusion bag containing 500 mL of 0.9% Sodium Chloride Injection, USP. Infuse continuously over 24 hours. Repeat daily for a total of 7 consecutive days. The use of 5% dextrose as a diluent is not recommended because of increased degradation of cladribine. Admixtures of cladribine injection, USP are chemically and physically stable for at least 24 hours at room temperature under normal room fluorescent light in Baxter Viaflex® PVC infusion containers. Since limited compatibility data are available, adherence to the recommended diluents and infusion systems is advised.

 | Dose of Cladribine Injection, USP | Recommended Diluent | Quantity of Diluent
24-hour infusion method | 1(day) × 0.09 mg/kg | 0.9% Sodium Chloride Injection, USP | 500 mL

To prepare a 7-day infusion

The 7-day infusion solution should only be prepared with Bacteriostatic 0.9% Sodium Chloride Injection, USP (0.9% benzyl alcohol preserved). In order to minimize the risk of microbial contamination, both cladribine injection, USP and the diluent should be passed through a sterile 0.22 µm disposable hydrophilic syringe filter as each solution is being introduced into the infusion reservoir. First add the calculated dose of cladribine injection, USP (7 days × 0.09 mg/kg or mL/kg) to the infusion reservoir through the sterile filter.

Then add a calculated amount of Bacteriostatic 0.9% Sodium Chloride Injection, USP (0.9% benzyl alcohol preserved) also through the filter to bring the total volume of the solution to 100 mL. After completing solution preparation, clamp off the line, disconnect and discard the filter. Aseptically aspirate air bubbles from the reservoir as necessary using the syringe and a dry second sterile filter or a sterile vent filter assembly. Reclamp the line and discard the syringe and filter assembly. Infuse continuously over 7 days. Solutions prepared with Bacteriostatic Sodium Chloride Injection for individuals weighing more than 85 kg may have reduced preservative effectiveness due to greater dilution of the benzyl alcohol preservative. Admixtures for the 7-day infusion have demonstrated acceptable chemical and physical stability for at least 7 days in the SIMS Deltec MEDICATION CASSETTE™ Reservoir.

 | Dose of Cladribine Injection, USP | Recommended Diluent | Quantity of Diluent
7-day infusion method (use sterile 0.22µ filter when preparing infusion solution) | 7 (days) × 0.09 mg/kg | Bacteriostatic 0.9% Sodium Chloride Injection, USP (0.9% benzyl alcohol) | q.s. to 100 mL

Since limited compatibility data are available, adherence to the recommended diluents and infusion systems is advised. Solutions containing cladribine injection, USP should not be mixed with other intravenous drugs or additives or infused simultaneously via a common intravenous line, since compatibility testing has not been performed. Preparations containing benzyl alcohol should not be used in neonates (see WARNINGS).

Care must be taken to assure the sterility of prepared solutions. Once diluted, solutions of cladribine injection, USP should be administered promptly or stored in the refrigerator (2° to 8° C) for no more than 8 hours prior to start of administration. Vials of cladribine injection, USP are for single-use only. Any unused portion should be discarded in an appropriate manner (see Handling and Disposal).

Parenteral drug products should be inspected visually for particulate matter and discoloration prior to administration, whenever solution and container permit. A precipitate may occur during the exposure of cladribine injection, USP to low temperatures; it may be resolubilized by allowing the solution to warm naturally to room temperature and by shaking vigorously. DO NOT HEAT OR MICROWAVE.

Chemical Stability of Vials

When stored in refrigerated conditions between 2° to 8°C (36° to 46°F) protected from light, unopened vials of cladribine injection, USP are stable until the expiration date indicated on the package. Freezing does not adversely affect the solution. If freezing occurs, thaw naturally to room temperature. DO NOT heat or microwave. Once thawed, the vial of cladribine injection, USP is stable until expiry if refrigerated. DO NOT refreeze. Once diluted, solutions containing cladribine injection, USP should be administered promptly or stored in the refrigerator (2° to 8°C) for no more than 8 hours prior to administration.

Handling and Disposal

The potential hazards associated with cytotoxic agents are well established and proper precautions should be taken when handling, preparing, and administering cladribine injection, USP. The use of disposable gloves and protective garments is recommended. If cladribine injection, USP contacts the skin or mucous membranes, wash the involved surface immediately with copious amounts of water. Several guidelines on this subject have been published.(2–8) There is no general agreement that all of the procedures recommended in the guidelines are necessary or appropriate. Refer to your Institution's guidelines and all applicable state/local regulations for disposal of cytotoxic waste.

HOW SUPPLIED

Cladribine Injection, USP is supplied as a sterile, preservative-free, isotonic solution containing 10 mg (1 mg/mL) of cladribine as 10 mL filled into a single-dose clear flint glass 20 mL vial, individually boxed. NDC 42658-010-01.

STORAGE AND HANDLING

Store refrigerated 2° to 8°C (36° to 46°F). Protect from light during storage.

REFERENCES

1. Santana VM, Mirro J, Harwood FC, et al: A phase I clinical trial of 2-Chloro-deoxyadenosine in pediatric patients with acute leukemia. J. Clin. Onc., 9: 416 (1991).
2. Recommendations for the Safe Handling of Parenteral Antineoplastic Drugs. NIH Publication No. 83-2621. For sale by the Superintendent of Documents, U. S. Government Printing Office, Washington, D. C. 20402.
3. AMA Council Report. Guidelines for Handling Parenteral Antineoplastics, JAMA, March 15 (1985).
4. National Study Commission on Cytotoxic Exposure--Recommendations for Handling Cytotoxic Agents. Available from Louis P. Jeffrey, Sc.D., Chairman, National Study Commission on Cytotoxic Exposure, Massachusetts College of Pharmacy and Allied Health Sciences, 179 Longwood Avenue, Boston, Massachusetts 02115.
5. Clinical Oncological Society of Australia: Guidelines and Recommendations for Safe Handling of Antineoplastic Agents, Med. J. Australia 1:425 (1983).
6. Jones RB, et al. Safe Handling of Chemotherapeutic Agents: A Report from the Mount Sinai Medical Center. Ca--A Cancer Journal for Clinicians, Sept/Oct. 258–263 (1983).
7. American Society of Hospital Pharmacists Technical Assistance Bulletin on Handling Cytotoxic Drugs in Hospitals. Am. J. Hosp. Pharm., 42:131 (1985).
8. OSHA Work-Practice Guidelines for Personnel Dealing with Cytotoxic (antineoplastic) Drugs. Am. J. Hosp. Pharm., 43:1193 (1986).

Distributed by:
Hisun Pharmaceuticals USA, Inc.
Bridgewater, NJ 08807 USA
Manufactured in China
Issued: 12/2019

PRINCIPAL DISPLAY PANEL - 10 mL Carton and Vial

10 mL
NDC 42658-010-01 Carton

NDC 42658-010-01 Vial